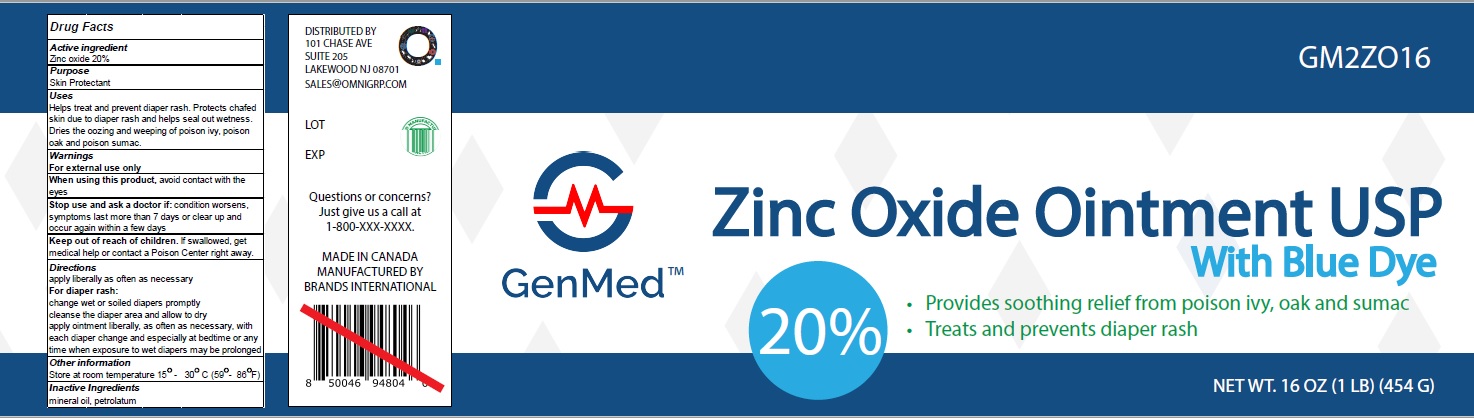 DRUG LABEL: ZINC OXIDE
NDC: 50157-333 | Form: OINTMENT
Manufacturer: ​BRANDS INTERNATIONAL
Category: otc | Type: HUMAN OTC DRUG LABEL
Date: 20230315

ACTIVE INGREDIENTS: ZINC OXIDE 20 g/100 g
INACTIVE INGREDIENTS: PETROLATUM; LIGHT MINERAL OIL

GenMed ZINC OXIDE Ointment USP with Blue Dye

Active ingredient

Zinc Oxide (20% w/w)

Purpose

Skin Protectant

Purpose

- helps treat and prevent diaper rash
- dries the oozing and weeping of poison ivy, poison oak, poison sumac

Warnings

For external use only

When using this product

- do not get into eyes
- do not use over large areas of the body

Keep out of reach of children

- if swallowed, get medical help or contact a Poison Control Center right away

Directions

- for diaper rash
- change wet and soiled diapers promptly
- cleanse the diaper area and allow to dry
- apply ointment liberally with each diaper change, especially at bedtime or any time when exposure to wet diapers may be prolonged
- for poison ivy, oak, sumac
- apply ointment liberally as often as needed

Other information

- store at 59°-86° F (15°-30°C)
- avoid excessive heat

Inactive ingredients

mineral oil, petrolatum